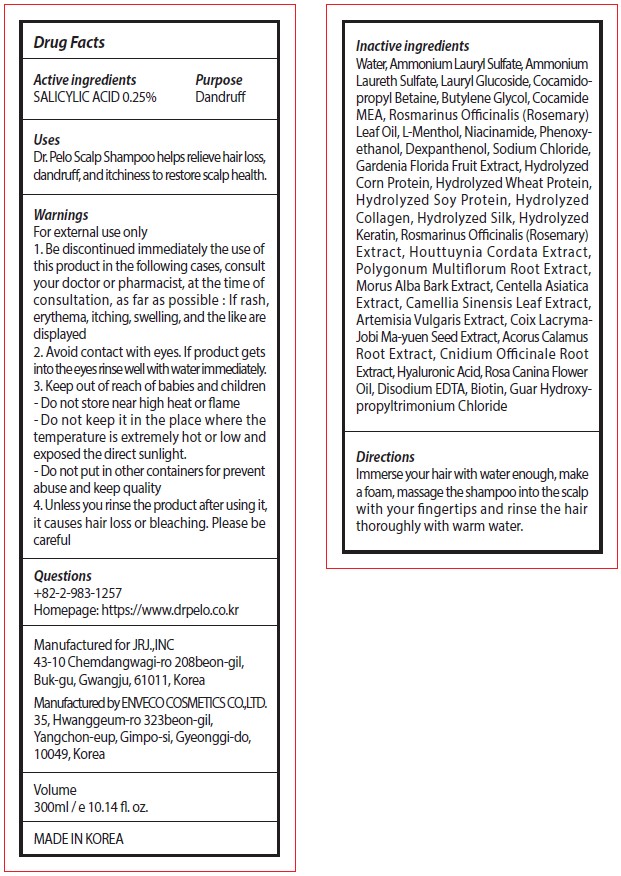 DRUG LABEL: Dr. Pelo Scalp-Shampoo
NDC: 81702-202 | Form: SHAMPOO
Manufacturer: JRJ.,INC
Category: otc | Type: HUMAN OTC DRUG LABEL
Date: 20210322

ACTIVE INGREDIENTS: SALICYLIC ACID 0.25 mg/100 mL
INACTIVE INGREDIENTS: BUTYLENE GLYCOL; DEXPANTHENOL; GARDENIA JASMINOIDES FRUIT; HYDROLYZED SOY PROTEIN (ENZYMATIC; 2000 MW); ROSEMARY; REYNOUTRIA MULTIFLORA ROOT; MORUS ALBA BARK; COIX LACRYMA-JOBI VAR. MA-YUEN SEED; HYALURONIC ACID; ROSA CANINA FLOWER OIL; GUAR HYDROXYPROPYLTRIMONIUM CHLORIDE (1.7 SUBSTITUENTS PER SACCHARIDE); SODIUM CHLORIDE; GREEN TEA LEAF; LAURYL GLUCOSIDE; LEVOMENTHOL; NIACINAMIDE; HYDROLYZED WHEAT PROTEIN (ENZYMATIC, 3000 MW); CENTELLA ASIATICA WHOLE; ARTEMISIA VULGARIS ROOT; ACORUS CALAMUS ROOT; CNIDIUM OFFICINALE ROOT; EDETATE DISODIUM ANHYDROUS; BIOTIN; WATER; COCO MONOETHANOLAMIDE; ROSEMARY OIL; PHENOXYETHANOL; AMMONIUM LAURYL SULFATE; COCAMIDOPROPYL BETAINE; HOUTTUYNIA CORDATA FLOWERING TOP

81702-202 Dr. Pelo Scalp Shampoo

Active ingredients

SALICYLIC ACID 0.25%

Purpose

Dandruff

Uses

Dr. Pelo Scalp Shampoo helps relieve hair loss, dandruff, and itchiness to restore scalp health.

Warnings

For external use only

4. Unless you rinse the product after using it, it causes hair loss or bleaching. Please be careful

Stop use

1. Be discontinued immediately the use of this product in the following cases, consult your doctor or pharmacist, at the time of consultation, as far as possible : If rash, erythema, itching, swelling, and the like are displayed
2. Avoid contact with eyes. If product gets into the eyes rinse well with water immediately.

Keep out of reach of children

3. Keep out of reach of babies and children

Other information

- Do not store near high heat or flame
- Do not keep it in the place where the temperature is extremely hot or low and exposed the direct sunlight.
- Do not put in other containers for prevent abuse and keep quality

Directions

Immerse your hair with water enough, make a foam, massage the shampoo into the scalp with your fingertips and rinse the hair thoroughly with warm water.

Inactive ingredients

Water, Ammonium Lauryl Sulfate, Ammonium Laureth Sulfate, Lauryl Glucoside, Cocamidopropyl Betaine, Butylene Glycol, Cocamide MEA, Rosmarinus Officinalis (Rosemary) Leaf Oil, L-Menthol, Niacinamide, Phenoxyethanol, Dexpanthenol, Sodium Chloride, Gardenia Florida Fruit Extract, Hydrolyzed Corn Protein, Hydrolyzed Wheat Protein, Hydrolyzed Soy Protein, Hydrolyzed
Collagen, Hydrolyzed Silk, Hydrolyzed Keratin, Rosmarinus Officinalis (Rosemary) Extract, Houttuynia Cordata Extract,
Polygonum Multiflorum Root Extract, Morus Alba Bark Extract, Centella Asiatica Extract, Camellia Sinensis Leaf Extract, Artemisia Vulgaris Extract, Coix Lacryma-Jobi Ma-yuen Seed Extract, Acorus Calamus Root Extract, Cnidium Officinale Root Extract, Hyaluronic Acid, Rosa Canina Flower Oil, Disodium EDTA, Biotin, Guar Hydroxypropyltrimonium Chloride